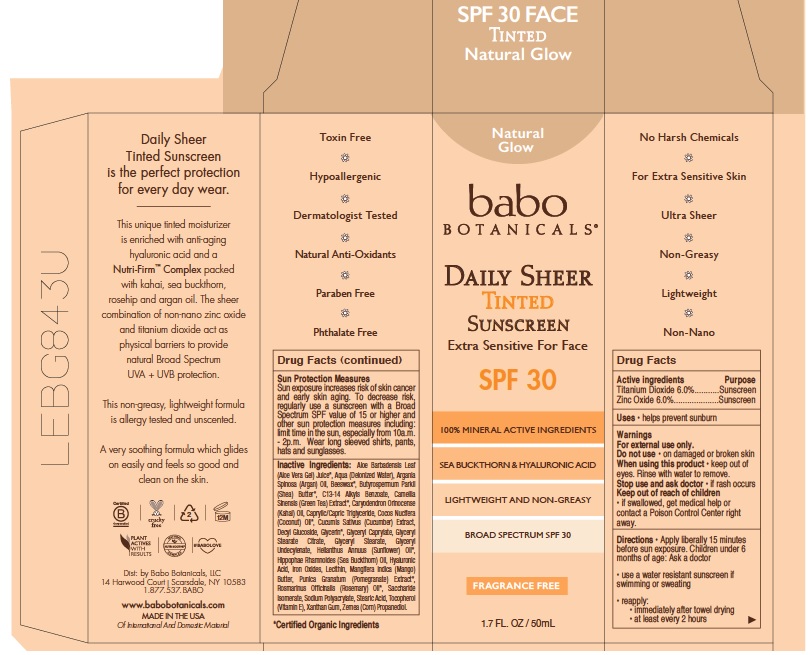 DRUG LABEL: Babo Botanicals SPF 30 Daily Sheer Tinted Sunscreen - Natural Glow
NDC: 79265-8072 | Form: LOTION
Manufacturer: Babo Botanicals, Inc.
Category: otc | Type: HUMAN OTC DRUG LABEL
Date: 20241212

ACTIVE INGREDIENTS: TITANIUM DIOXIDE 3000 mg/100 mL; ZINC OXIDE 3000 mg/100 mL
INACTIVE INGREDIENTS: WATER 27.803 mL/100 mL; GREEN TEA LEAF 0.2 mL/100 mL; ROSEMARY 0.05 mL/100 mL; XANTHAN GUM 0.05 mL/100 mL; PROPANEDIOL 10 mL/100 mL; YELLOW WAX 0.05 mL/100 mL; SHEA BUTTER 1 mL/100 mL; ALKYL (C12-15) BENZOATE 5.5 mL/100 mL; CARYODENDRON ORINOCENSE WHOLE 0.1 mL/100 mL; MEDIUM-CHAIN TRIGLYCERIDES 5.5 mL/100 mL; GLYCERYL STEARATE CITRATE 1.5 mL/100 mL; COCONUT OIL 3 mL/100 mL; CUCUMBER SEED 0.2 mL/100 mL; GLYCERIN 1 mL/100 mL; GLYCERYL 1-UNDECYLENATE 0.45 mL/100 mL; ALOE VERA LEAF 10 mL/100 mL; DECYL GLUCOSIDE 8.7 mL/100 mL; FERRIC OXIDE RED 1.547 mL/100 mL; LECITHIN, SUNFLOWER 3.5 mL/100 mL; MANGO 0.25 mL/100 mL; SACCHARIDE ISOMERATE 0.15 mL/100 mL; STEARIC ACID 1 mL/100 mL; ALPHA-TOCOPHEROL 0.1 mL/100 mL; SODIUM POLYACRYLATE (8000 MW) 0.2 mL/100 mL; GLYCERYL CAPRYLATE 0.45 mL/100 mL; ARGAN OIL 0.2 mL/100 mL; GLYCERYL MONOSTEARATE 2 mL/100 mL; SUNFLOWER OIL 3 mL/100 mL; HYALURONIC ACID 0.1 mL/100 mL; HIPPOPHAE RHAMNOIDES SEED OIL 0.2 mL/100 mL; POMEGRANATE 0.2 mL/100 mL

8072 Babo SPF 30 Daily Sheer Tinted

This is a sunscreen manufactured according to the 2009 Final Monograph

The sunscreen is manufactured using only approved mineral active ingredients of Zinc Oxide (6%) and Titanium Oxide (6%) in the preparation of the product (percentage in final product formulation) consistent with The Final Monograph.

Active Ingredient(s)

Zinc Oxide 6% Purpose: Sunscreen

Titanium Dioxide 6% Purpose: Sunscreen

Purpose

Sunscreen

Uses

Uses• Helps prevent sunburn.

Warnings

For external use only.

Do not use

on damaged or broken skin

WHEN USING

Keep out of eyes. Rinse with water to remove.

Stop use and ask doctor if rash occurs.

Keep out of reach of children. If swallowed get medical help or contact a Poison Control center right away.

Directions

Apply liberally15 minutes before sun exposure. Children under 6 months of age: Ask a doctor.

• use a water resistant sunscreen if swimming or sweating• reapply: • immediately after towel drying • at least every 2 hours

Sun Protection Measures

Sun exposure increases risk of skin cancer and early skin aging. To decrease risk, regularly use a sunscreen with a Broad Spectrum SPF value of 15 or higher and other sun protection measures including: limit time in the sun, especially from 10a.m. - 2p.m. Wear long sleeved shirts, pants, hats and sunglasses.

Inactive ingredients

Aloe Barbadensis Leaf (Aloe Vera Gel) Juice*, Aqua (Deionized Water), Argania Spinosa (Argan) Oil, Beeswax*, Butyrospermum Parkii (Shea) Butter*, C13-14 Alkyls Benzoate, Camellia Sinensis (Green Tea) Extract*, Caryodendron Orinocense (Kahai) Oil, Caprylic/Capric Triglyceride, Cocos Nucifera (Coconut) Oil*, Cucumis Sativus (Cucumber) Extract, Decyl Glucoside, Glycerin*, Glyceryl Caprylate, Glyceryl Stearate Citrate, Glyceryl Stearate, Glyceryl Undecylenate, Helianthus Annuus (Sunflower) Oil*, Hippophae Rhamnoides (Sea Buckthorn) Oil, Hyaluronic Acid, Iron Oxides, Lecithin, Mangifera Indica (Mango) Butter, Punica Granatum (Pomegranate) Extract*, Rosmarinus Officinalis (Rosemary) Oil*, Saccharide Isomerate, Sodium Polyacrylate, Stearic Acid, Tocopherol (Vitamin E), Xanthan Gum, Zemea (Corn) Propanediol.

*Certified Organic ingredients

Package Label - Principal Display Panel

50 mL NDC: 79265-8072-1 Outer packaging